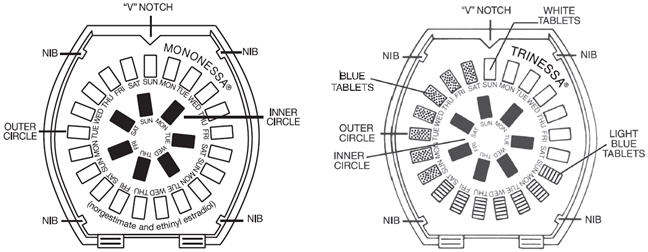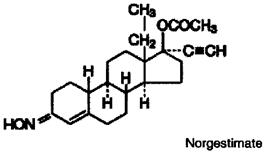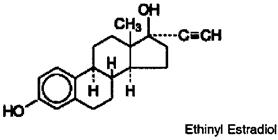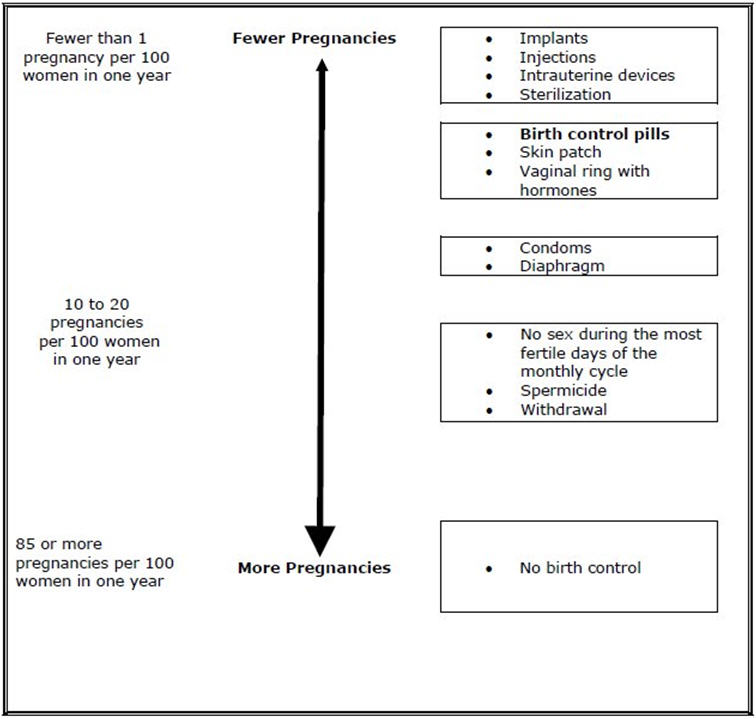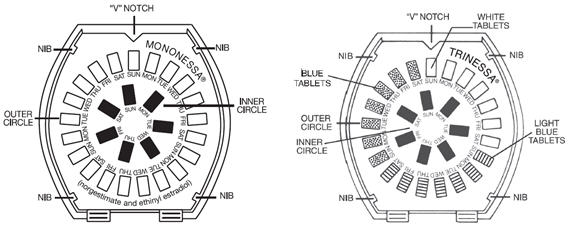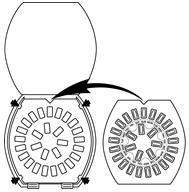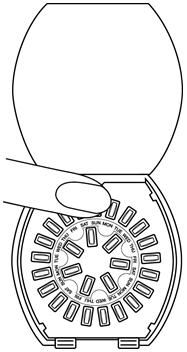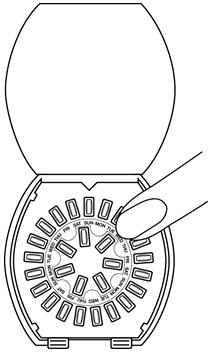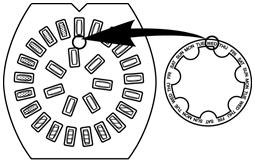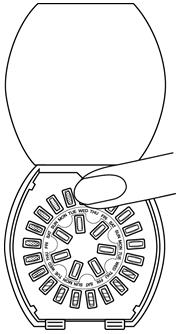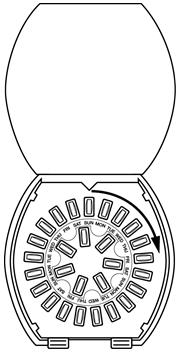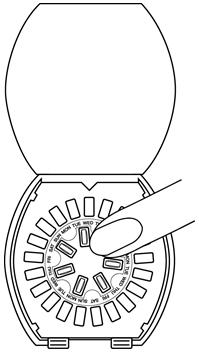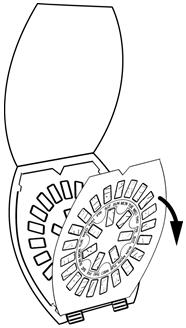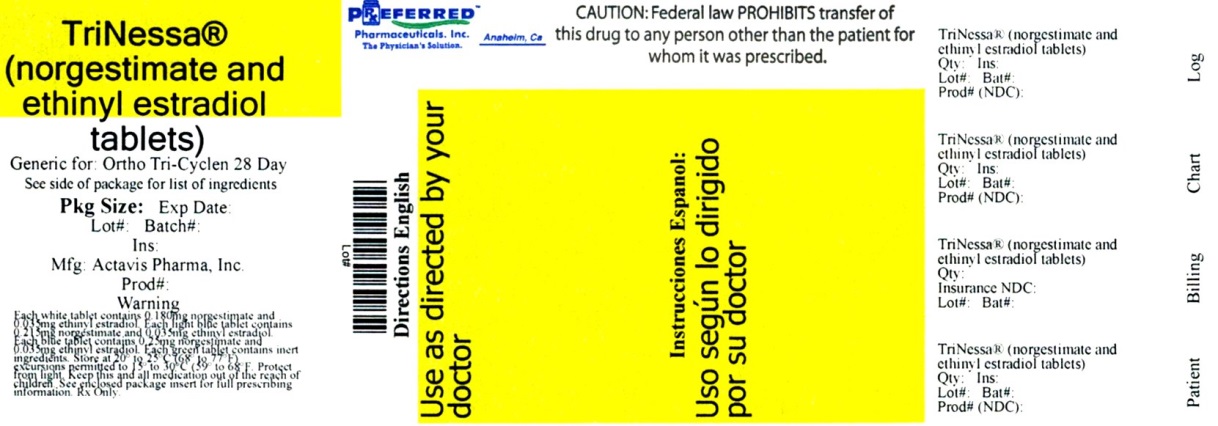 DRUG LABEL: TriNessa
NDC: 68788-7239 | Form: KIT | Route: ORAL
Manufacturer: Preferred Pharmaceuticals Inc,
Category: prescription | Type: HUMAN PRESCRIPTION DRUG LABEL
Date: 20190412

ACTIVE INGREDIENTS: norgestimate 0.18 mg/1 1; ethinyl estradiol 0.035 mg/1 1; norgestimate 0.215 mg/1 1; ethinyl estradiol 0.035 mg/1 1; norgestimate 0.25 mg/1 1; ethinyl estradiol 0.035 mg/1 1
INACTIVE INGREDIENTS: CARNAUBA WAX; CROSCARMELLOSE SODIUM; HYPROMELLOSE, UNSPECIFIED; LACTOSE, UNSPECIFIED FORM; MAGNESIUM STEARATE; MICROCRYSTALLINE CELLULOSE; POLYETHYLENE GLYCOL, UNSPECIFIED; TITANIUM DIOXIDE; WATER; FD&C BLUE No. 2; ALUMINUM OXIDE; CARNAUBA WAX; CROSCARMELLOSE SODIUM; HYPROMELLOSE, UNSPECIFIED; LACTOSE, UNSPECIFIED FORM; MAGNESIUM STEARATE; MICROCRYSTALLINE CELLULOSE; POLYETHYLENE GLYCOL, UNSPECIFIED; TITANIUM DIOXIDE; WATER; FD&C BLUE No. 2; ALUMINUM OXIDE; CARNAUBA WAX; CROSCARMELLOSE SODIUM; HYPROMELLOSE, UNSPECIFIED; LACTOSE, UNSPECIFIED FORM; MAGNESIUM STEARATE; MICROCRYSTALLINE CELLULOSE; POLYETHYLENE GLYCOL, UNSPECIFIED; POLYSORBATE 80; TITANIUM DIOXIDE; WATER; FD&C BLUE NO. 2; ALUMINUM OXIDE; FERRIC OXIDE RED; POLYVINYL ALCOHOL, UNSPECIFIED; LACTOSE, UNSPECIFIED FORM; MAGNESIUM STEARATE; POLYETHYLENE GLYCOL, UNSPECIFIED; STARCH, CORN; TALC; TITANIUM DIOXIDE; WATER

HIGHLIGHTS OF PRESCRIBING INFORMATION

These highlights do not include all the information needed to use MonoNessa or TriNessa safely and effectively. See full prescribing information for MonoNessa and TriNessa.
MonoNessa® and TriNessa® (norgestimate/ethinyl estradiol) tablets, for oral use
Initial U.S. Approval: 1989

WARNING: CIGARETTE SMOKING and SERIOUS CARDIOVASCULAR EVENTS

See full prescribing information for complete boxed warning.

- MonoNessa or TriNessa is contraindicated in women over 35 years old who smoke. (4)
- Cigarette smoking increases the risk of serious cardiovascular events from combination oral contraceptives (COC) use. (4)

RECENT MAJOR CHANGES

Contraindications (4) | 08/2017
Warnings and Precautions (5.3) | 08/2017

1 INDICATIONS AND USAGE

MonoNessa and TriNessa are estrogen/progestin COCs, indicated for use by women to prevent pregnancy. (1.1)

TriNessa is also indicated for the treatment of moderate acne vulgaris in females at least 15 years of age, who have no known contraindications to oral contraceptive therapy and have achieved menarche.

TriNessa should be used for the treatment of acne only if the patient desires an oral contraceptive for birth control. (1.2)

2 DOSAGE AND ADMINISTRATION

- Take one tablet daily by mouth at the same time every day. (2.2)
- Take tablets in the order directed on the blister pack. (2.2)
- Do not skip or delay tablet intake. (2.2)

3 DOSAGE FORMS AND STRENGTHS

MonoNessa consists of 28 round, biconvex, coated tablets in the following order (3):

- 21 blue tablets each containing 0.250 mg norgestimate and 0.035 mg ethinyl estradiol
- 7 dark green tablets (inert)

TriNessa consists of 28 round, biconvex, coated tablets in the following order (3):

- 7 white tablets each containing 0.180 mg norgestimate and 0.035 mg ethinyl estradiol
- 7 light blue tablets each containing 0.215 mg norgestimate and 0.035 mg ethinyl estradiol
- 7 blue tablets each containing 0.250 mg norgestimate and 0.035 mg ethinyl estradiol
- 7 dark green tablets (inert)

4 CONTRAINDICATIONS

- A high risk of arterial or venous thrombotic diseases (4)
- Liver tumors or liver disease (4)
- Undiagnosed abnormal uterine bleeding (4)
- Pregnancy (4)
- Breast cancer or other estrogen- or progestin-sensitive cancer (4)
- Co-administration with Hepatitis C drug combinations containing ombitasvir/paritaprevir/ritonavir, with or without dasabuvir (4)

5 WARNINGS AND PRECAUTIONS

- Thromboembolic Disorders and Other Vascular Problems: Stop MonoNessa or TriNessa if a thrombotic event occurs. Stop at least 4 weeks before and through 2 weeks after major surgery. Start no earlier than 4 weeks after delivery, in women who are not breastfeeding. (5.1)
- Liver disease: Discontinue MonoNessa or TriNessa if jaundice occurs. (5.2)
- High blood pressure: If used in women with well-controlled hypertension, monitor blood pressure and stop MonoNessa or TriNessa if blood pressure rises significantly. (5.4)
- Carbohydrate and lipid metabolic effects: Monitor prediabetic and diabetic women taking MonoNessa or TriNessa. Consider an alternate contraceptive method for women with uncontrolled dyslipidemia. (5.6)
- Headache: Evaluate significant change in headaches and discontinue MonoNessa or TriNessa if indicated. (5.7)
- Bleeding Irregularities and Amenorrhea: Evaluate irregular bleeding or amenorrhea. (5.8)

6 ADVERSE REACTIONS

The most common adverse reactions reported during clinical trials (≥2%) were:

MonoNessa: headache/migraine, abdominal/gastrointestinal pain, vaginal infection, genital discharge, breast issues (including breast pain, discharge, and enlargement), mood disorders (including depression and mood altered), flatulence, nervousness, rash. (6.1)

TriNessa: headache/migraine, breast issues (including breast pain, enlargement, and discharge), vaginal infection, abdominal/gastrointestinal pain, mood disorders (including mood alteration and depression), genital discharge, changes in weight (including weight increased or decreased). (6.1)To report SUSPECTED ADVERSE REACTIONS, contact Actavis at 1-800-272-5525 or FDA at 1-800-FDA-1088 or www.fda.gov/medwatch.

7 DRUG INTERACTIONS

Drugs or herbal products that induce certain enzymes including CYP3A4, may decrease the effectiveness of COCs or increase breakthrough bleeding. Counsel patients to use a back-up or alternative method of contraception when enzyme inducers are used with COCs. (7.1)

8 USE IN SPECIFIC POPULATIONS

Nursing mothers: Not recommended; can decrease milk production. (8.3)

FULL PRESCRIBING INFORMATION

WARNING: CIGARETTE SMOKING and SERIOUS CARDIOVASCULAR EVENTS

Cigarette smoking increases the risk of serious cardiovascular events from combination oral contraceptive (COC) use. This risk increases with age, particularly in women over 35 years of age, and with the number of cigarettes smoked. For this reason, COCs are contraindicated in women who are over 35 years of age and smoke [see Contraindications (4)].

1 INDICATIONS AND USAGE

1.1 Oral Contraceptive

MonoNessa and TriNessa Tablets are indicated for use by females of reproductive potential to prevent pregnancy [see Clinical Studies (14)].

1.2 Acne

TriNessa is indicated for the treatment of moderate acne vulgaris in females at least 15 years of age, who have no known contraindications to oral contraceptive therapy and have achieved menarche. TriNessa should be used for the treatment of acne only if the patient desires an oral contraceptive for birth control [see Clinical Studies (14)].

2 DOSAGE AND ADMINISTRATION

2.1 How to Start MonoNessa or TriNessa

MonoNessa and TriNessa are dispensed in a VERIDATE Tablet Dispenser [see How Supplied/Storage and Handling (16)]. MonoNessa and TriNessa may be started using either a Day 1 start or a Sunday start (see Table 1). For the first cycle of a Sunday Start regimen, an additional method of contraception should be used until after the first 7 consecutive days of administration.

2.2 How to Take MonoNessa or TriNessa

Table 1: Instructions for Administration of MonoNessa or TriNessa
Starting COCs in women not currently using hormonal contraception (Day 1 Start or Sunday Start) Important: Consider the possibility of ovulation and conception prior to initiation of this product. Tablet Color:; - MonoNessa active tablets are blue (Day 1 to Day 21). - TriNessa active tablets are white (Day 1 to Day 7), light blue (Day 8 to Day 14) and blue (Day 15 to Day 21). - MonoNessa and TriNessa both have dark green inactive tablets (Day 22 to Day 28). | Day 1 Start:; - Take first active tablet without regard to meals on the first day of menses. - Take subsequent active tablets once daily at the same time each day for a total of 21 days. - Take one dark green inactive tablet daily for 7 days and at the same time of day that active tablets were taken. - Begin each subsequent pack on the same day of the week as the first cycle pack (i.e., on the day after taking the last inactive tablet)
Starting COCs in women not currently using hormonal contraception (Day 1 Start or Sunday Start) Important: Consider the possibility of ovulation and conception prior to initiation of this product. Tablet Color:; - MonoNessa active tablets are blue (Day 1 to Day 21). - TriNessa active tablets are white (Day 1 to Day 7), light blue (Day 8 to Day 14) and blue (Day 15 to Day 21). - MonoNessa and TriNessa both have dark green inactive tablets (Day 22 to Day 28). | Sunday Start:; - Take first active tablet without regard to meals on the first Sunday after the onset of menses. Due to the potential risk of becoming pregnant, use additional non-hormonal contraception (such as condoms and spermicide) for the first seven days of the patient's first cycle pack of MonoNessa or TriNessa. - Take subsequent active tablets once daily at the same time each day for a total of 21 days. - Take one dark green inactive tablet daily for the following 7 days and at the same time of day that active tablets were taken. - Begin each subsequent pack on the same day of the week as the first cycle pack (i.e., on the Sunday after taking the last inactive tablet) and additional non-hormonal contraceptive is not needed.
Switching to MonoNessa or TriNessa from another oral contraceptive | Start on the same day that a new pack of the previous oral contraceptive would have started.
Switching from another contraceptive method to MonoNessa or TriNessa | Start MonoNessa or TriNessa:
- Transdermal patch | - On the day when next application would have been scheduled
- Vaginal ring | - On the day when next insertion would have been scheduled
- Injection | - On the day when next injection would have been scheduled
- Intrauterine contraceptive | - On the day of removal - If the IUD is not removed on first day of the patient's menstrual cycle, additional non-hormonal contraceptive (such as condoms and spermicide) is needed for the first seven days of the first cycle pack.
- Implant | - On the day of removal
Complete instructions to facilitate patient counseling on proper tablet usage are located in the FDA-Approved Patient Labeling.

Starting MonoNessa or TriNessa after Abortion or Miscarriage

First-trimester

- After a first-trimester abortion or miscarriage, MonoNessa or TriNessa may be started immediately. An additional method of contraception is not needed if MonoNessa or TriNessa is started immediately.
- If MonoNessa or TriNessa is not started within 5 days after termination of the pregnancy, the patient should use additional non-hormonal contraception (such as condoms and spermicide) for the first seven days of her first cycle pack of MonoNessa or TriNessa.

Second-trimester

- Do not start until 4 weeks after a second-trimester abortion or miscarriage, due to the increased risk of thromboembolic disease. Start MonoNessa or TriNessa, following the instructions in Table 1 for Day 1 or Sunday start, as desired. If using Sunday start, use additional non-hormonal contraception (such as condoms and spermicide) for the first seven days of the patient's first cycle pack of MonoNessa or TriNessa. [see Contraindications (4), Warnings and Precautions (5.1), and FDA-Approved Patient Labeling.]

Starting MonoNessa or TriNessa after Childbirth

- Do not start until 4 weeks after delivery, due to the increased risk of thromboembolic disease. Start contraceptive therapy with MonoNessa or TriNessa following the instructions in Table 1 for women not currently using hormonal contraception.
- MonoNessa or TriNessa are not recommended for use in lactating women [see Use in Specific Populations (8.3)].
- If the woman has not yet had a period postpartum, consider the possibility of ovulation and conception occurring prior to use of MonoNessa or TriNessa. [See Contraindications (4), Warnings and Precautions (5.1), Use in Specific Populations (8.1 and 8.3), and FDA-Approved Patient Labeling].

VERIDATE® Tablet Dispenser

- Place the refill in the VERIDATE Tablet Dispenser so that the V notch in the refill is at the top of the dispenser. Press the refill down so that it fits firmly under all the nibs (see illustration below).
- If the patient starts pill-taking on Sunday, the first active pill should be taken on the first Sunday after the patient's menstrual period begins. Remove the first active pill at the top of the dispenser (Sunday) by pressing the pill through the hole in the bottom of the dispenser.

MonoNessa:

- If the patient will start pill-taking on "Day 1," choose a blue pill that corresponds with the day of the week the patient will take the first pill. Remove that blue pill by pressing the pill through the hole in the bottom of the dispenser.

TriNessa:

- If the patient will start pill-taking on a day other than Sunday, a calendar label has been provided and should be placed over the calendar in the center of the VERIDATE. To place the label correctly, identify the correct starting day, locate that day printed in blue on the label, and line that day up with the first white pill directly under the V notch at the top of the dispenser. Remove the label from the backing. Press the center of the label down onto the center of the printed calendar. Remove that white pill by pressing the pill through the hole in the bottom of the dispenser.
- After all the dark green pills have been taken, insert a new refill into the VERIDATE. The patient should take the first pill on the next day, even if the patient's period is not over yet.

To Insert New Refill (MonoNessa or TriNessa):

- Lift the empty refill out of the VERIDATE Tablet Dispenser.
- Insert the new refill so that the V notch in the refill is at the top of the dispenser. Press the refill down so that it fits firmly under the nibs.

2.3 Missed Tablets

Table 2: Instructions for Missed MonoNessa or TriNessa Tablets
- If one active tablet is missed in Weeks 1, 2, or 3 | Take the tablet as soon as possible. Continue taking one tablet a day until the pack is finished.
- If two active tablets are missed in Week 1 or Week 2 | Take the two missed tablets as soon as possible and the next two active tablets the next day. Continue taking one tablet a day until the pack is finished. Additional non-hormonal contraception (such as condoms and spermicide) should be used as back-up if the patient has sex within 7 days after missing tablets.
- If two active tablets are missed in the third week or three or more active tablets are missed in a row in Weeks 1, 2, or 3 | Day 1 start: Throw out the rest of the pack and start a new pack that same day. Sunday start: Continue taking one tablet a day until Sunday, then throw out the rest of the pack and start a new pack that same day. Additional non-hormonal contraception (such as condoms and spermicide) should be used as back-up if the patient has sex within 7 days after missing tablets.

2.4 Advice in Case of Gastrointestinal Disturbances

In case of severe vomiting or diarrhea, absorption may not be complete and additional contraceptive measures should be taken. If vomiting or diarrhea occurs within 3 to 4 hours after taking an active tablet, handle this as a missed tablet [see FDA-Approved Patient Labeling].

2.5 TriNessa Use for Acne

The timing of initiation of dosing with TriNessa for acne should follow the guidelines for use of TriNessa as an oral contraceptive. Consult the DOSAGE AND ADMINISTRATION section (2.1) for instructions.

3 DOSAGE FORMS AND STRENGTHS

MonoNessa:

MonoNessa Tablets are available in blister cards. Each blister card contains 28 tablets in the following order:

- 21 blue, round, biconvex, coated tablet imprinted "WPI" on one side and "526" on the other side of the tablet contains 0.250 mg norgestimate and 0.035 mg ethinyl estradiol
- 7 dark green round, biconvex, coated tablet (non-hormonal placebo) imprinted "WPI" on one side and "P" on the other side contains inert ingredients

TriNessa:

TriNessa Tablets are available in blister cards. Each blister card contains 28 tablets in the following order:

- 7 white, round, biconvex, coated tablet imprinted "WPI" on one side and "524" on the other side of the tablet contains 0.180 mg norgestimate and 0.035 mg ethinyl estradiol
- 7 light blue, round, biconvex, coated tablet imprinted "WPI" on one side and "525" on the other side of the tablet contains 0.215 mg norgestimate and 0.035 mg ethinyl estradiol
- 7 blue, round, biconvex, coated tablet imprinted "WPI" on one side and "526" on the other side of the tablet contains 0.250 mg norgestimate and 0.035 mg ethinyl estradiol
- 7 dark green round, biconvex, coated tablet (non-hormonal placebo) imprinted "WPI" on one side and "P" on the other side contains inert ingredients

4 CONTRAINDICATIONS

Do not prescribe MonoNessa or TriNessa to women who are known to have the following conditions:

- A high risk of arterial or venous thrombotic diseases. Examples include women who are known to:
  - Smoke, if over age 35 [see Boxed Warning and Warnings and Precautions (5.1)]
  - Have deep vein thrombosis or pulmonary embolism, now or in the past [see Warnings and Precautions (5.1)]
  - Have inherited or acquired hypercoagulopathies [see Warnings and Precautions (5.1)]
  - Have cerebrovascular disease [see Warnings and Precautions (5.1)]
  - Have coronary artery disease [see Warnings and Precautions (5.1)]
  - Have thrombogenic valvular or thrombogenic rhythm diseases of the heart (for example, subacute bacterial endocarditis with valvular disease, or atrial fibrillation) [see Warnings and Precautions (5.1)]
  - Have uncontrolled hypertension [see Warnings and Precautions (5.4)]
  - Have diabetes mellitus with vascular disease [see Warnings and Precautions (5.6)]
  - Have headaches with focal neurological symptoms or migraine headaches with aura [see Warnings and Precautions (5.7)]
    - Women over age 35 with any migraine headaches [see Warnings and Precautions (5.7)]
- Liver tumors, benign or malignant, or liver disease [see Warnings and Precautions (5.2)]
- Undiagnosed abnormal uterine bleeding [see Warnings and Precautions (5.8)]
- Pregnancy, because there is no reason to use COCs during pregnancy [see Warnings and Precautions (5.9) and Use in Specific Populations (8.1)]
- Breast cancer or other estrogen- or progestin-sensitive cancer, now or in the past [see Warnings and Precautions (5.11)]
- Use of Hepatitis C drug combinations containing ombitasvir/paritaprevir/ritonavir, with or without dasabuvir, due to the potential for ALT elevations [see Warnings and Precautions (5.3)]

5 WARNINGS AND PRECAUTIONS

5.1 Thromboembolic Disorders and Other Vascular Problems

- Stop MonoNessa or TriNessa if an arterial thrombotic event or venous thromboembolic (VTE) event occurs.
- Stop MonoNessa or TriNessa if there is unexplained loss of vision, proptosis, diplopia, papilledema, or retinal vascular lesions. Evaluate for retinal vein thrombosis immediately [see Adverse Reactions (6.2)].
- If feasible, stop MonoNessa or TriNessa at least 4 weeks before and through 2 weeks after major surgery or other surgeries known to have an elevated risk of VTE as well as during and following prolonged immobilization.
- Start MonoNessa or TriNessa no earlier than 4 weeks after delivery, in women who are not breastfeeding. The risk of postpartum VTE decreases after the third postpartum week, whereas the risk of ovulation increases after the third postpartum week.
- The use of COCs increases the risk of VTE. However, pregnancy increases the risk of VTE as much or more than the use of COCs. The risk of VTE in women using COCs is 3 to 9 cases per 10,000 woman-years. The risk of VTE is highest during the first year of use of COCs and when restarting hormonal contraception after a break of 4 weeks or longer. The risk of thromboembolic disease due to COCs gradually disappears after use is discontinued.
- Use of COCs also increases the risk of arterial thromboses such as strokes and myocardial infarctions, especially in women with other risk factors for these events. COCs have been shown to increase both the relative and attributable risks of cerebrovascular events (thrombotic and hemorrhagic strokes). This risk increases with age, particularly in women over 35 years of age who smoke.
- Use COCs with caution in women with cardiovascular disease risk factors.

5.2 Liver Disease

Impaired Liver Function

Do not use MonoNessa or TriNessa in women with liver disease, such as acute viral hepatitis or severe (decompensated) cirrhosis of liver [see Contraindications (4)]. Acute or chronic disturbances of liver function may necessitate the discontinuation of COC use until markers of liver function return to normal and COC causation has been excluded. Discontinue MonoNessa or TriNessa if jaundice develops.

Liver Tumors

MonoNessa and TriNessa are contraindicated in women with benign and malignant liver tumors [see Contraindications (4)]. Hepatic adenomas are associated with COC use. An estimate of the attributable risk is 3.3 cases/100,000 COC users. Rupture of hepatic adenomas may cause death through intra-abdominal hemorrhage.

Studies have shown an increased risk of developing hepatocellular carcinoma in long-term (>8 years) COC users. However, the risk of liver cancers in COC users is less than one case per million users.

5.3 Risk of Liver Enzyme Elevations with Concomitant Hepatitis C Treatment

During clinical trials with the Hepatitis C combination drug regimen that contains ombitasvir/paritaprevir/ritonavir, with or without dasabuvir, ALT elevations greater than 5 times the upper limit of normal (ULN), including some cases greater than 20 times the ULN, were significantly more frequent in women using ethinyl estradiol-containing medications, such as COCs. Discontinue MonoNessa or TriNessa prior to starting therapy with the combination drug regimen ombitasvir/paritaprevir/ritonavir, with or without dasabuvir [see Contraindications (4)]. MonoNessa or TriNessa can be restarted approximately 2 weeks following completion of treatment with the Hepatitis C combination drug regimen.

5.4 High Blood Pressure

MonoNessa and TriNessa are contraindicated in women with uncontrolled hypertension or hypertension with vascular disease [see Contraindications (4)]. For women with well-controlled hypertension, monitor blood pressure and stop MonoNessa and TriNessa if blood pressure rises significantly.

An increase in blood pressure has been reported in women taking COCs, and this increase is more likely in older women with extended duration of use. The incidence of hypertension increases with increasing concentrations of progestin.

5.5 Gallbladder Disease

Studies suggest a small increased relative risk of developing gallbladder disease among COC users. Use of COCs may worsen existing gallbladder disease. A past history of COC-related cholestasis predicts an increased risk with subsequent COC use. Women with a history of pregnancy-related cholestasis may be at an increased risk for COC related cholestasis.

5.6 Carbohydrate and Lipid Metabolic Effects

Carefully monitor prediabetic and diabetic women who take MonoNessa or TriNessa. COCs may decrease glucose tolerance.

Consider alternative contraception for women with uncontrolled dyslipidemia. A small proportion of women will have adverse lipid changes while on COCs.

Women with hypertriglyceridemia, or a family history thereof, may be at an increased risk of pancreatitis when using COCs.

5.7 Headache

If a woman taking MonoNessa or TriNessa develops new headaches that are recurrent, persistent, or severe, evaluate the cause and discontinue MonoNessa or TriNessa if indicated.

Consider discontinuation of MonoNessa or TriNessa in the case of increased frequency or severity of migraine during COC use (which may be prodromal of a cerebrovascular event).

5.8 Bleeding Irregularities and Amenorrhea

Unscheduled Bleeding and Spotting

Unscheduled (breakthrough or intracyclic) bleeding and spotting sometimes occur in patients on COCs, especially during the first three months of use. If bleeding persists or occurs after previously regular cycles, check for causes such as pregnancy or malignancy. If pathology and pregnancy are excluded, bleeding irregularities may resolve over time or with a change to a different contraceptive product.

In clinical trials of MonoNessa and TriNessa, the frequency and duration of breakthrough bleeding and/or spotting was assessed in 1,647 patients (21,275 evaluable cycles) and 4,826 patients (35,546 evaluable cycles), respectively. A total of 100 (7.5%) women discontinued MonoNessa and 231 (4.8%) women discontinued TriNessa, at least in part, due to bleeding or spotting. Based on data from the clinical trials, 14–34% of women using MonoNessa experienced unscheduled bleeding per cycle in the first year; for TriNessa, the respective numbers were 13–38%. The percent of women who experienced breakthrough/unscheduled bleeding tended to decrease over time.

Amenorrhea and Oligomenorrhea

Women who use MonoNessa or TriNessa may experience amenorrhea. Some women may experience amenorrhea or oligomenorrhea after discontinuation of COCs, especially when such a condition was pre-existent.

If scheduled (withdrawal) bleeding does not occur, consider the possibility of pregnancy. If the patient has not adhered to the prescribed dosing schedule (missed one or more active tablets or started taking them on a day later than she should have), consider the possibility of pregnancy at the time of the first missed period and take appropriate diagnostic measures. If the patient has adhered to the prescribed regimen and misses two consecutive periods, rule out pregnancy.

5.9 COC Use Before or During Early Pregnancy

Extensive epidemiological studies have revealed no increased risk of birth defects in women who have used oral contraceptives prior to pregnancy. Studies also do not suggest a teratogenic effect, particularly in so far as cardiac anomalies and limb reduction defects are concerned, when oral contraceptives are taken inadvertently during early pregnancy. Discontinue MonoNessa or TriNessa use if pregnancy is confirmed.

Administration of COCs to induce withdrawal bleeding should not be used as a test for pregnancy [see Use in Specific Populations (8.1)].

5.10 Depression

Carefully observe women with a history of depression and discontinue MonoNessa or TriNessa if depression recurs to a serious degree.

5.11 Carcinoma of Breast and Cervix

- MonoNessa and TriNessa are contraindicated in women who currently have or have had breast cancer because breast cancer may be hormonally sensitive [see Contraindications (4)].
There is substantial evidence that COCs do not increase the incidence of breast cancer. Although some past studies have suggested that COCs might increase the incidence of breast cancer, more recent studies have not confirmed such findings.
- Some studies suggest that COC use has been associated with an increase in the risk of cervical cancer or intraepithelial neoplasia. However, there continues to be controversy about the extent to which such findings may be due to differences in sexual behavior and other factors.

5.12 Effect on Binding Globulins

The estrogen component of COCs may raise the serum concentrations of thyroxine-binding globulin, sex hormone-binding globulin, and cortisol-binding globulin. The dose of replacement thyroid hormone or cortisol therapy may need to be increased.

5.13 Monitoring

A woman who is taking COCs should have a yearly visit with her healthcare provider for a blood pressure check and for other indicated healthcare.

5.14 Hereditary Angioedema

In women with hereditary angioedema, exogenous estrogens may induce or exacerbate symptoms of angioedema.

5.15 Chloasma

Chloasma may occasionally occur, especially in women with a history of chloasma gravidarum. Women with a tendency to chloasma should avoid exposure to the sun or ultraviolet radiation while taking MonoNessa or TriNessa.

6 ADVERSE REACTIONS

The following serious adverse reactions with the use of COCs are discussed elsewhere in labeling:

- Serious cardiovascular events and stroke [see Boxed Warning and Warnings and Precautions (5.1)]
- Vascular events [see Warnings and Precautions (5.1)]
- Liver disease [see Warnings and Precautions (5.2)]

Adverse reactions commonly reported by COC users are:

- Irregular uterine bleeding
- Nausea
- Breast tenderness
- Headache

6.1 Clinical Trial Experience

Because clinical trials are conducted under widely varying conditions, adverse reaction rates observed in the clinical trials of a drug cannot be directly compared to rates in the clinical trials of another drug and may not reflect the rates observed in clinical practice.

MonoNessa

The safety of MonoNessa was evaluated in 1,647 healthy women of child-bearing potential who participated in 3 clinical trials and received at least 1 dose of MonoNessa for contraception. Two trials were randomized active-controlled trials and 1 was an uncontrolled open-label trial. In all 3 trials, subjects were followed for up to 24 cycles.

Common Adverse Reactions (≥ 2% of subjects): The most common adverse reactions reported by at least 2% of the 1,647 women were the following in order of decreasing incidence: headache/migraine (32.9%), abdominal/gastrointestinal pain (7.8%), vaginal infection (8.4%), genital discharge (6.8%), breast issues (including breast pain, discharge, and enlargement) (6.3%), mood disorders (including depression and mood altered) (5.0%), flatulence (3.2%), nervousness (2.9%), and rash (2.6%).

Adverse Reactions Leading to Study Discontinuation: Over the three trials, between 11 to 21% of subjects discontinued the trial due to an adverse reaction. The most common adverse reactions (≥1%) leading to discontinuation were: metrorrhagia (6.9%), nausea/vomiting (5.0%), headache (4.1%), mood disorders (including depression and mood altered) (2.4%), premenstrual syndrome (1.7%), hypertension (1.4%), breast pain (1.4%), nervousness (1.3%), amenorrhea (1.1%), dysmenorrhea (1.1%), weight increased (1.1%), and flatulence (1.1%).

Serious Adverse Reactions: breast cancer (1 subject), mood disorders including depression, irritability, and mood swings (1 subject), myocardial infarction (1 subject), and venous thromboembolic events including pulmonary embolism (1 subject) and deep vein thrombosis (DVT) (1 subject).

TriNessa

The safety of TriNessa was evaluated in 4,826 healthy women of child-bearing potential who participated in 6 clinical trials and received at least 1 dose of TriNessa for contraception. Two trials were randomized active-controlled trials and 4 were uncontrolled open-label trials. In 3 trials, subjects were followed for up to 24 cycles; in 2 trials, subjects were followed for up to 12 cycles; and in 1 trial, subjects were followed for up to 6 cycles.

Common Adverse Reactions (≥ 2% of subjects): The most common adverse reactions reported by at least 2% of the 4,826 women were the following in order of decreasing incidence: headache/migraine (33.6%), breast issues (including breast pain, enlargement, and discharge) (8.0%), vaginal infection (7.1%), abdominal/gastrointestinal pain (5.6%), mood disorders (including mood alteration and depression) (3.8%), genital discharge (3.2%), and changes in weight (including weight fluctuation, increased or decreased) (2.5%).

Adverse Reactions Leading to Study Discontinuation: Over the trials, between 9 to 27% of subjects discontinued the trial due to an adverse reaction. The most common adverse reactions (≥1%) leading to discontinuation were: metrorrhagia (4.3%), nausea/vomiting (2.8%), headache/migraine (2.4%), mood disorders (including depression and mood altered) (1.1%), and weight increased (1.1%).

Serious Adverse Reactions: breast cancer (1 subject), carcinoma of the cervix in situ (1 subject), hypertension (1 subject), and migraine (2 subjects).

6.2 Postmarketing Experience

The following additional adverse drug reactions have been reported from worldwide postmarketing experience with norgestimate/ethinyl estradiol. Because these reactions are reported voluntarily from a population of uncertain size, it is not always possible to reliably estimate their frequency or establish a causal relationship to drug exposure.

Infections and Infestations: Urinary tract infection;

Neoplasms Benign, Malignant and Unspecified (Incl. Cysts and Polyps): Breast cancer, benign breast neoplasm, hepatic adenoma, focal nodular hyperplasia, breast cyst;

Immune System Disorders: Hypersensitivity;

Metabolism and Nutrition Disorders: Dyslipidemia;

Psychiatric Disorders: Anxiety, insomnia;

Nervous System Disorders: Syncope, convulsion, paresthesia, dizziness;

Eye Disorders: Visual impairment, dry eye, contact lens intolerance;

Ear and Labyrinth Disorders: Vertigo;

Cardiac Disorders: Tachycardia, palpitations;

Vascular Events: Deep vein thrombosis, pulmonary embolism, retinal vascular thrombosis, hot flush, venous thrombosis (including Budd Chiari Syndrome and hepatic vein thrombosis);

Arterial Events: Arterial thromboembolism, myocardial infarction, cerebrovascular accident;

Respiratory, Thoracic and Mediastinal Disorders: Dyspnea;

Gastrointestinal Disorders: Pancreatitis, abdominal distension, diarrhea, constipation;

Hepatobiliary Disorders: Hepatitis;

Skin and Subcutaneous Tissue Disorders: Angioedema, erythema nodosum, hirsutism, night sweats, hyperhidrosis, photosensitivity reaction, urticaria, pruritus, acne;

Musculoskeletal, Connective Tissue, and Bone Disorders: Muscle spasms, pain in extremity, myalgia, back pain;

Reproductive System and Breast Disorders: Ovarian cyst, suppressed lactation, vulvovaginal dryness;

General Disorders and Administration Site Conditions: Chest pain, asthenic conditions.

7 DRUG INTERACTIONS

Consult the labeling of concurrently used drugs to obtain further information about interactions with hormonal contraceptives or the potential for enzyme alterations.

No drug-drug interaction studies were conducted with MonoNessa or TriNessa.

7.1 Effects of Other Drugs on Combined Oral Contraceptives

Substances decreasing the plasma concentrations of COCs:

Drugs or herbal products that induce certain enzymes, including cytochrome P450 3A4 (CYP3A4), may decrease the plasma concentrations of COCs and potentially diminish the effectiveness of COCs or increase breakthrough bleeding. Some drugs or herbal products that may decrease the effectiveness of hormonal contraceptives include phenytoin, barbiturates, carbamazepine, bosentan, felbamate, griseofulvin, oxcarbazepine, rifampicin, topiramate, rifabutin, rufinamide, aprepitant, and products containing St. John's wort. Interactions between hormonal contraceptives and other drugs may lead to breakthrough bleeding and/or contraceptive failure. Counsel women to use an alternative method of contraception or a back-up method when enzyme inducers are used with COCs, and to continue back-up contraception for 28 days after discontinuing the enzyme inducer to ensure contraceptive reliability.

Colesevelam: Colesevelam, a bile acid sequestrant, given together with a COC, has been shown to significantly decrease the AUC of EE. The drug interaction between the contraceptive and colesevelam was decreased when the two drug products were given 4 hours apart.

Substances increasing the plasma concentrations of COCs:

Co-administration of atorvastatin or rosuvastatin and certain COCs containing ethinyl estradiol (EE) increase AUC values for EE by approximately 20–25%. Ascorbic acid and acetaminophen may increase plasma EE concentrations, possibly by inhibition of conjugation. CYP3A4 inhibitors such as itraconazole, voriconazole, fluconazole, grapefruit juice, or ketoconazole may increase plasma hormone concentrations.

Human immunodeficiency virus (HIV)/Hepatitis C virus (HCV) protease inhibitors and non-nucleoside reverse transcriptase inhibitors:

Significant changes (increase or decrease) in the plasma concentrations of estrogen and/or progestin have been noted in some cases of co-administration with HIV protease inhibitors (decrease [e.g., nelfinavir, ritonavir, darunavir/ritonavir, (fos)amprenavir/ritonavir, lopinavir/ritonavir, and tipranavir/ritonavir] or increase [e.g., indinavir and atazanavir/ritonavir])/HCV protease inhibitors (decrease [e.g., boceprevir and telaprevir]) or with non-nucleoside reverse transcriptase inhibitors (decrease [e.g., nevirapine] or increase [e.g., etravirine]).

7.2 Effects of Combined Oral Contraceptives on Other Drugs

- COCs containing EE may inhibit the metabolism of other compounds (e.g., cyclosporine, prednisolone, theophylline, tizanidine, and voriconazole) and increase their plasma concentrations.
- COCs have been shown to decrease plasma concentrations of acetaminophen, clofibric acid, morphine, salicylic acid, temazepam and lamotrigine. Significant decrease in plasma concentration of lamotrigine has been shown, likely due to induction of lamotrigine glucuronidation. This may reduce seizure control; therefore, dosage adjustments of lamotrigine may be necessary.
Women on thyroid hormone replacement therapy may need increased doses of thyroid hormone because the serum concentration of thyroid-binding globulin increases with use of COCs.

7.3 Interference with Laboratory Tests

The use of contraceptive steroids may influence the results of certain laboratory tests, such as coagulation factors, lipids, glucose tolerance, and binding proteins.

7.4 Concomitant Use with HCV Combination Therapy – Liver Enzyme Elevation

Do not co-administer MonoNessa or TriNessa with HCV drug combinations containing ombitasvir/paritaprevir/ritonavir, with or without dasabuvir, due to potential for ALT elevations [see Warnings and Precautions (5.3)].

8 USE IN SPECIFIC POPULATIONS

8.1 Pregnancy

There is little or no increased risk of birth defects in women who inadvertently use COCs during early pregnancy. Epidemiologic studies and meta-analyses have not found an increased risk of genital or non-genital birth defects (including cardiac anomalies and limb reduction defects) following exposure to low dose COCs prior to conception or during early pregnancy.

Do not administer COCs to induce withdrawal bleeding as a test for pregnancy. Do not use COCs during pregnancy to treat threatened or habitual abortion.

8.3 Nursing Mothers

Advise the nursing mother to use other forms of contraception, when possible, until she has weaned her child. COCs can reduce milk production in breastfeeding mothers. This is less likely to occur once breastfeeding is well-established; however, it can occur at any time in some women. Small amounts of oral contraceptive steroids and/or metabolites are present in breast milk.

8.4 Pediatric Use

Safety and efficacy of MonoNessa Tablets and TriNessa Tablets have been established in women of reproductive age. Efficacy is expected to be the same for post-pubertal adolescents under the age of 18 and for users 18 years and older. Use of this product before menarche is not indicated.

There was no significant difference between TriNessa Tablets and placebo in mean change in total lumbar spine (L1–L4) and total hip bone mineral density between baseline and Cycle 13 in 123 adolescent females with anorexia nervosa in a double-blind, placebo-controlled, multicenter, one-year treatment duration clinical trial for the Intent To Treat (ITT) population.

8.5 Geriatric Use

MonoNessa and TriNessa have not been studied in postmenopausal women and are not indicated in this population.

8.6 Hepatic Impairment

The pharmacokinetics of MonoNessa and TriNessa have not been studied in subjects with hepatic impairment. However, steroid hormones may be poorly metabolized in patients with hepatic impairment. Acute or chronic disturbances of liver function may necessitate the discontinuation of COC use until markers of liver function return to normal and COC causation has been excluded. [See Contraindications (4) and Warnings and Precautions (5.2).]

8.7 Renal Impairment

The pharmacokinetics of MonoNessa and TriNessa have not been studied in women with renal impairment.

10 OVERDOSAGE

There have been no reports of serious ill effects from overdosage of oral contraceptives, including ingestion by children. Overdosage may cause withdrawal bleeding in females and nausea.

11 DESCRIPTION

Each of the following products is a combination oral contraceptive containing the progestational compound norgestimate and the estrogenic compound ethinyl estradiol. Norgestimate is designated as (18,19-Dinor-17-pregn-4-en-20-yn-3-one,17-(acetyloxy)-13-ethyl-, oxime,(17α)-(+)-) and ethinyl estradiol is designated as (19-nor-17α-pregna,1,3,5(10)-trien-20-yne-3,17-diol).

MonoNessa

- Each active blue tablet contains 0.250 mg of norgestimate and 0.035 mg of ethinyl estradiol. Inactive ingredients include carnauba wax, croscarmellose sodium, FD & C Blue No. 2 Aluminum Lake, hypromellose, lactose, magnesium stearate, microcrystalline cellulose, polyethylene glycol, polysorbate 80, purified water, and titanium dioxide.
- Each dark green placebo tablet containing only inert ingredients, as follows: FD & C Blue No. 2 Aluminum Lake, ferric oxide, lactose, magnesium stearate, polyethylene glycol, pregelatinized corn starch, purified water, polyvinyl alcohol, talc, and titanium dioxide.

TriNessa

- Each active white tablet contains 0.180 mg of norgestimate and 0.035 mg of ethinyl estradiol. Inactive ingredients include carnauba wax, croscarmellose sodium, hypromellose, lactose, magnesium stearate, microcrystalline cellulose, polyethylene glycol, purified water, and titanium dioxide.
- Each active light blue tablet contains 0.215 mg of norgestimate and 0.035 mg of ethinyl estradiol. Inactive ingredients include carnauba wax, croscarmellose sodium, FD & C Blue No. 2 Aluminum Lake, hypromellose, lactose, magnesium stearate, microcrystalline cellulose, polyethylene glycol, purified water, and titanium dioxide.
- Each active blue tablet contains 0.250 mg of norgestimate and 0.035 mg of ethinyl estradiol. Inactive ingredients include carnauba wax, croscarmellose sodium, FD & C Blue No. 2 Aluminum Lake, hypromellose, lactose, magnesium stearate, microcrystalline cellulose, polyethylene glycol, polysorbate 80, purified water, and titanium dioxide.
- Each dark green placebo tablet contains only inert ingredients, as follows: FD & C Blue No. 2 Aluminum Lake, ferric oxide, lactose, magnesium stearate, polyethylene glycol, pregelatinized corn starch, purified water, polyvinyl alcohol, talc, and titanium dioxide.

12 CLINICAL PHARMACOLOGY

12.1 Mechanism of Action

- Oral Contraception
  COCs lower the risk of becoming pregnant primarily by suppressing ovulation. Other possible mechanisms may include cervical mucus changes that inhibit sperm penetration and endometrial changes that reduce the likelihood of implantation.
- Acne
  Acne is a skin condition with a multifactorial etiology, including androgen stimulation of sebum production. While the combination of ethinyl estradiol and norgestimate increases sex hormone-binding globulin (SHBG) and decreases free testosterone, the relationship between these changes and a decrease in the severity of facial acne in otherwise healthy women with this skin condition has not been established.

12.2 Pharmacodynamics

No specific pharmacodynamic studies were conducted with MonoNessa or TriNessa.

12.3 Pharmacokinetics

Absorption

Norgestimate (NGM) and EE are rapidly absorbed following oral administration. NGM is rapidly and completely metabolized by first pass (intestinal and/or hepatic) mechanisms to norelgestromin (NGMN) and norgestrel (NG), which are the major active metabolites of norgestimate.

Peak serum concentrations of NGMN and EE are generally reached by 2 hours after administration of MonoNessa or TriNessa. Accumulation following multiple dosing of the 250 mcg NGM / 35 mcg EE dose is approximately 2-fold for NGMN and EE compared with single dose administration. The pharmacokinetics of NGMN is dose-proportional following NGM doses of 180 mcg to 250 mcg. Steady-state concentration of EE is achieved by Day 7 of each dosing cycle. Steady-state concentrations of NGMN and NG are achieved by Day 21. Non-linear accumulation (approximately 8 fold) of NG is observed as a result of high-affinity binding to SHBG, which limits its biological activity (Table 3).

Table 3: Summary of NGMN, NG and EE pharmacokinetic parameters.
Mean (SD) Pharmacokinetic Parameters of TriNessa During a Three Cycle Study
Analyte | Cycle | Day | Cmax | tmax (h) | AUC0–24h | t1/2 (h)
NGMN | 3 | 7 | 1.80 (0.46) | 1.42 (0.73) | 15.0 (3.88) | NC
 |  | 14 | 2.12 (0.56) | 1.21 (0.26) | 16.1 (4.97) | NC
 |  | 21 | 2.66 (0.47) | 1.29 (0.26) | 21.4 (3.46) | 22.3 (6.54)
NG | 3 | 7 | 1.94 (0.82) | 3.15 (4.05) | 34.8 (16.5) | NC
 |  | 14 | 3.00 (1.04) | 2.21 (2.03) | 55.2 (23.5) | NC
 |  | 21 | 3.66 (1.15) | 2.58 (2.97) | 69.3 (23.8) | 40.2 (15.4)
EE | 3 | 7 | 124 (39.5) | 1.27 (0.26) | 1130 (420) | NC
 |  | 14 | 128 (38.4) | 1.32 (0.25) | 1130 (324) | NC
 |  | 21 | 126 (34.7) | 1.31 (0.56) | 1090 (359) | 15.9 (4.39)
Mean (SD) Pharmacokinetic Parameters of MonoNessa During a Three Cycle Study
Analyte | Cycle | Day | Cmax | tmax (h) | AUC0–24h | t1/2 (h)
NGMN | 1 | 1 | 1.78 (0.397) | 1.19 (0.250) | 9.90 (3.25) | 18.4 (5.91)
 | 3 | 21 | 2.19 (0.655) | 1.43 (0.680) | 18.1 (5.53) | 24.9 (9.04)
NG | 1 | 1 | 0.649 (0.49) | 1.42 (0.69) | 6.22 (2.46) | 37.8 (14.0)
 | 3 | 21 | 2.65 (1.11) | 1.67 (1.32) | 48.2 (20.5) | 45.0 (20.4)
EE | 1 | 1 | 92.2 (24.5) | 1.2 (0.26) | 629 (138) | 10.1 (1.90)
 | 3 | 21 | 147 (41.5) | 1.13 (0.23) | 1210 (294) | 15.0 (2.36)
Cmax = peak serum concentration, tmax = time to reach peak serum concentration, AUC0–24h = area under serum concentration vs time curve from 0 to 24 hours, t1/2 = elimination half-life, NC = not calculated.
NGMN and NG: Cmax = ng/mL, AUC0–24h = h∙ng/mL
EE: Cmax = pg/mL, AUC0–24h = h∙pg/mL

Food Effect

The effect of food on the pharmacokinetics of MonoNessa or TriNessa has not been studied.

Distribution

NGMN and NG are highly bound (>97%) to serum proteins. NGMN is bound to albumin and not to SHBG, while NG is bound primarily to SHBG. EE is extensively bound (>97%) to serum albumin and induces an increase in the serum concentrations of SHBG.

Metabolism

NGM is extensively metabolized by first-pass mechanisms in the gastrointestinal tract and/or liver. NGM's primary active metabolite is NGMN. Subsequent hepatic metabolism of NGMN occurs and metabolites include NG, which is also active, and various hydroxylated and conjugated metabolites. Although NGMN and its metabolites inhibit a variety of P450 enzymes in human liver microsomes, under the recommended dosing regimen, the in vivo concentrations of NGMN and its metabolites, even at the peak serum levels, are relatively low compared to the inhibitory constant (Ki). EE is also metabolized to various hydroxylated products and their glucuronide and sulfate conjugates.

Excretion

The metabolites of NGMN and EE are eliminated by renal and fecal pathways. Following administration of ^14C-norgestimate, 47% (45–49%) and 37% (16–49%) of the administered radioactivity was eliminated in the urine and feces, respectively. Unchanged NGM was not detected in the urine. In addition to 17-deacetyl norgestimate, a number of metabolites of NGM have been identified in human urine following administration of radiolabeled NGM. These include 18, 19-Dinor-17-pregn-4-en-20-yn-3-one,17-hydroxy-13-ethyl,(17α)-(-);18,19-Dinor-5β-17-pregnan-20-yn,3α,17β-dihydroxy-13-ethyl,(17α), various hydroxylated metabolites and conjugates of these metabolites.

13 NONCLINICAL TOXICOLOGY

13.1 Carcinogenesis, Mutagenesis, Impairment of Fertility

[See Warnings and Precautions (5.2, 5.11) and Use in Specific Populations (8.1).]

14 CLINICAL STUDIES

14.1 Contraception

In three US clinical trials with MonoNessa, 1,651 women aged 18 to 38 years were studied for up to 24 cycles, proving a total of 24,272 cycles of exposure. The racial demographic was about 73–86% Caucasian, 8–13% African-American, 6–14% Hispanic with the remainder Asian or Other (≤1%). There were no exclusions on the basis of weight; the weight range for women treated was 82–303 lbs, with a mean weight of about 135 lbs. The pregnancy rate was approximately 1 pregnancy per 100 women-years.

In four clinical trials with TriNessa, 4,756 women aged 15 to 41 years were studied for 24 cycles, providing a total of 45,244 cycles of exposure. The racial demographic was about 87–90% Caucasian, 6–10% African-American, with the remainder Asian (≤1%) or Other (2–5%). There were no exclusions on the basis of weight; the weight range for women treated was 80–310 lbs, with a mean weight of about 132 lbs. The pregnancy rate was approximately 1 pregnancy per 100 women-years.

14.2 Acne

TriNessa was evaluated for the treatment of acne vulgaris in two randomized, double-blind, placebo-controlled, multicenter, six- (28 day) cycle studies. Two hundred twenty-one patients received TriNessa and 234 patients received placebo. Mean age at enrollment for both groups was 28 years. At the end of 6 months, the mean total lesion count changed from 55 to 31 (42% reduction) in patients treated with TriNessa and from 54 to 38 (27% reduction) in patients similarly treated with placebo. Table 4 summarizes the changes in lesion count for each type of lesion. Based on the investigator's global assessment conducted at the final visit, patients treated with TriNessa showed a statistically significant improvement in total lesions compared to those treated with placebo.

Table 4:Acne Vulgaris Indication. Combined Results: Two Multicenter, Placebo-Controlled Trials. Observed Means at Six Months (LOCF) [LOCF: Last Observation Carried Forward] and at Baseline. Intent-to-Treat Population.
 | TriNessa (N=221) |  | Placebo (N=234) |  | Difference in Counts between TriNessa and Placebo at 6 Months
# of Lesions | Counts | % Reduction | Counts | % Reduction
INFLAMMATORY LESIONS
Baseline Mean | 19 |  | 19
Sixth Month Mean | 10 | 48% | 13 | 30% | 3 (95% CI: -1.2, 5.1)
NON-INFLAMMATORY LESIONS
Baseline Mean | 36 |  | 35
Sixth Month Mean | 22 | 34% | 25 | 21% | 3 (95% CI: -0.2, 7.8)
TOTAL LESIONS
Baseline Mean | 55 |  | 54 |  | 7 (95% CI: 2.0, 11.9)
Sixth Month Mean | 31 | 42% | 38 | 27%

16 HOW SUPPLIED/STORAGE AND HANDLING

16.1 How Supplied

TriNessa

TriNessa Tablets are available in a blister card with a VERIDATE Tablet Dispenser (unfilled) and VERIDATE refills: (NDC 68788-7239-2)

Each blister card (28 tablets) contains in the following order:

- 7 white, round, biconvex, coated tablet imprinted "WPI" on one side and "524" on the other side of the tablet contains 0.180 mg norgestimate and 0.035 mg ethinyl estradiol
- 7 light blue, round, biconvex, coated tablet imprinted "WPI" on one side and "525" on the other side of the tablet contains 0.215 mg norgestimate and 0.035 mg ethinyl estradiol
- 7 blue, round, biconvex, coated tablet imprinted "WPI" on one side and "526" on the other side of the tablet contains 0.250 mg norgestimate and 0.035 mg ethinyl estradiol
- 7 dark green round, biconvex, coated tablet (non-hormonal placebo) imprinted "WPI" on one side and "P" on the other side contains inert ingredients

16.2 Storage Conditions

- Store at 20–25°C (68–77°F); excursions permitted to 15° to 30°C (59° to 86°F).
- Protect from light.
- Keep out of the reach of children.

17 PATIENT COUNSELING INFORMATION

See FDA-approved patient labeling (Patient Information and Instructions for Use).

Counsel patients about the following information:

- Cigarette smoking increases the risk of serious cardiovascular events from COC use, and that women who are over 35 years old and smoke should not use COCs [see Boxed Warning].
- Increased risk of VTE compared to non-users of COCs is greatest after initially starting a COC or restarting (following a 4-week or greater pill-free interval) the same or a different COC [see Warnings and Precautions (5.1)].
- MonoNessa and TriNessa do not protect against HIV infection (AIDS) and other sexually transmitted infections.
- MonoNessa and TriNessa are not to be used during pregnancy; if pregnancy occurs during use of MonoNessa or TriNessa instruct the patient to stop further use [see Warnings and Precautions (5.9)].
- Take one tablet daily by mouth at the same time every day. Instruct patients what to do in the event tablets are missed [see Dosage and Administration (2.2)].
- Use a back-up or alternative method of contraception when enzyme inducers are used with MonoNessa or TriNessa [see Drug Interactions (7.1)].
- COCs may reduce breast milk production; this is less likely to occur if breastfeeding is well established [see Use in Specific Populations (8.3)].
- Women who start COCs postpartum, and who have not yet had a period, should use an additional method of contraception until they have taken an active tablet for 7 consecutive days [see Dosage and Administration (2.2)].
- Amenorrhea may occur. Consider pregnancy in the event of amenorrhea at the time of the first missed period. Rule out pregnancy in the event of amenorrhea in two or more consecutive cycles [see Warnings and Precautions (5.8)].

Manufactured by:
JOLLC
Manati, Puerto Rico 00674

Distributed by:
Actavis Pharma, Inc.
Parsippany, NJ 07054 USA

© 2015 Actavis Pharma, Inc.

Patient Information MonoNessa [mä-nō-nes-a] TriNessa [trī-nes-a] (norgestimate and ethinyl estradiol) Tablets

What is the most important information I should know about MonoNessa or TriNessa?

Do not use MonoNessa or TriNessa if you smoke cigarettes and are over 35 years old. Smoking increases your risk of serious cardiovascular side effects from hormonal birth control pills, including death from heart attack, blood clots or stroke. This risk increases with age and the number of cigarettes you smoke.

What is MonoNessa or TriNessa?

MonoNessa or TriNessa is a birth control pill (oral contraceptive) used by women to prevent pregnancy.

TriNessa is also used to treat moderate acne vulgaris in females 15 years of age and older, who have no known history of allergies or problems taking birth control pills, and have started their menstrual cycle ("period"). TriNessa should only be used to treat acne in women who want to take birth control pills to prevent pregnancy.

How does MonoNessa or TriNessa work for contraception?

Your chance of getting pregnant depends on how well you follow the directions for taking your birth control pills. The better you follow the directions, the less chance you have of getting pregnant.

Based on the results of clinical studies, about 1 out of 100 women may get pregnant during the first year they use MonoNessa or TriNessa.

The following chart shows the chance of getting pregnant for women who use different methods of birth control. Each box on the chart contains a list of birth control methods that are similar in effectiveness. The most effective methods are at the top of the chart. The box on the bottom of the chart shows the chance of getting pregnant for women who do not use birth control and are trying to get pregnant.

Who should not take MonoNessa or TriNessa?

Do not take MonoNessa or TriNessa if you:

- smoke and are over 35 years of age
- had blood clots in your arms, legs, lungs, or eyes
- had a problem with your blood that makes it clot more than normal
- have certain heart valve problems or irregular heart beat that increases your risk of having blood clots
- had a stroke
- had a heart attack
- have high blood pressure that cannot be controlled by medicine
- have diabetes with kidney, eye, nerve, or blood vessel damage
- have certain kinds of severe migraine headaches with aura, numbness, weakness or changes in vision, or any migraine headaches if you are over 35 years of age
- have liver problems, including liver tumors
- take any Hepatitis C drug combination containing ombitasvir/paritaprevir/ritonavir, with or without dasabuvir. This may increase levels of the liver enzyme "alanine aminotransferase" (ALT) in the blood.
- have any unexplained vaginal bleeding
- are pregnant
- had breast cancer or any cancer that is sensitive to female hormones

If any of these conditions happen while you are taking MonoNessa or TriNessa, stop taking MonoNessa or TriNessa right away and talk to your healthcare provider. Use non-hormonal contraception when you stop taking MonoNessa or TriNessa.

What should I tell my healthcare provider before taking MonoNessa or TriNessa?

Tell your healthcare provider if you:

- are pregnant or think you may be pregnant
- are depressed now or have been depressed in the past
- had yellowing of your skin or eyes (jaundice) caused by pregnancy (cholestasis of pregnancy)
- are breastfeeding or plan to breastfeed. MonoNessa or TriNessa may decrease the amount of breast milk you make. A small amount of the hormones in MonoNessa or TriNessa may pass into your breast milk. Talk to your healthcare provider about the best birth control method for you while breastfeeding.

Tell your healthcare provider about all the medicines you take, including prescription and over-the-counter medicines, vitamins and herbal supplements.

MonoNessa or TriNessa may affect the way other medicines work, and other medicines may affect how well MonoNessa or TriNessa works.

Know the medicines you take. Keep a list of them to show your healthcare provider and pharmacist when you get a new medicine.

How should I take MonoNessa or TriNessa?

Read the Instructions for Use at the end of this Patient Information.

What are the possible serious side effects of MonoNessa or TriNessa?

- Like pregnancy, MonoNessa or TriNessa may cause serious side effects, including blood clots in your lungs, heart attack, or a stroke that may lead to death. Some other examples of serious blood clots include blood clots in the legs or eyes.

Serious blood clots can happen especially if you smoke, are obese, or are older than 35 years of age. Serious blood clots are more likely to happen when you:

- first start taking birth control pills
- restart the same or different birth control pills after not using them for a month or more

Call your healthcare provider or go to a hospital emergency room right away if you have:

- leg pain that will not go away
- sudden severe shortness of breath
- sudden change in vision or blindness
- chest pain
- a sudden, severe headache unlike your usual headaches
- weakness or numbness in your arm or leg
- trouble speaking

Other serious side effects include:

- liver problems, including:
  - rare liver tumors
  - jaundice (cholestasis), especially if you previously had cholestasis of pregnancy. Call your healthcare provider if you have yellowing of your skin or eyes.
- high blood pressure. You should see your healthcare provider for a yearly check of your blood pressure.
- gallbladder problems
- changes in the sugar and fat (cholesterol and triglycerides) levels in your blood
- new or worsening headaches including migraine headaches
- irregular or unusual vaginal bleeding and spotting between your menstrual periods, especially during the first 3 months of taking MonoNessa or TriNessa.
- depression
- possible cancer in your breast and cervix
- swelling of your skin especially around your mouth, eyes, and in your throat (angioedema). Call your healthcare provider if you have a swollen face, lips, mouth tongue or throat, which may lead to difficulty swallowing or breathing. Your chance of having angioedema is higher is you have a history of angioedema.
- dark patches of skin around your forehead, nose, cheeks and around your mouth, especially during pregnancy (chloasma). Women who tend to get chloasma should avoid spending a long time in sunlight, tanning booths, and under sun lamps while taking MonoNessa or TriNessa. Use sunscreen if you have to be in the sunlight.

What are the most common side effects of MonoNessa or TriNessa?

- headache (migraine)
- breast pain or tenderness, enlargement or discharge
- stomach pain, discomfort, and gas
- vaginal infections and discharge
- mood changes, including depression
- nervousness
- changes in weight
- skin rash

These are not all the possible side effects of MonoNessa or TriNessa. For more information, ask your healthcare provider or pharmacist.

You may report side effects to the FDA at 1-800-FDA-1088.

What else should I know about taking MonoNessa or TriNessa?

- If you are scheduled for any lab tests, tell your healthcare provider you are taking MonoNessa or TriNessa. Certain blood tests may be affected by MonoNessa or TriNessa.
- MonoNessa or TriNessa does not protect against HIV infection (AIDS) and other sexually transmitted infections.

How should I store MonoNessa or TriNessa?

- Store MonoNessa or TriNessa at room temperature between 68°F to 77°F (20°C to 25°C).
- Keep MonoNessa or TriNessa and all medicines out of the reach of children.
- Store away from light.

General information about the safe and effective use of MonoNessa or TriNessa.

Medicines are sometimes prescribed for purposes other than those listed in a Patient Information leaflet. Do not use MonoNessa or TriNessa for a condition for which it was not prescribed. Do not give MonoNessa or TriNessa to other people, even if they have the same symptoms that you have.

This Patient Information summarizes the most important information about MonoNessa or TriNessa. You can ask your pharmacist or healthcare provider for information about MonoNessa or TriNessa that is written for health professionals.

For more information, call 1-800-272-5525.

Do birth control pills cause cancer?

Birth control pills do not seem to cause breast cancer. However, if you have breast cancer now, or have had it in the past, do not use birth control pills because some breast cancers are sensitive to hormones.

Women who use birth control pills may have a slightly higher chance of getting cervical cancer. However, this may be due to other reasons such as having more sexual partners.

What if I want to become pregnant?

You may stop taking the pill whenever you wish. Consider a visit with your healthcare provider for a pre-pregnancy checkup before you stop taking the pill.

What should I know about my period when taking MonoNessa or TriNessa?

Your periods may be lighter and shorter than usual. Some women may miss a period. Irregular vaginal bleeding or spotting may happen while you are taking MonoNessa or TriNessa, especially during the first few months of use. This usually is not a serious problem. It is important to continue taking your pills on a regular schedule to prevent a pregnancy.

What are the ingredients in MonoNessa or TriNessa?

MonoNessa:

Active ingredients: Each blue pill contains norgestimate and ethinyl estradiol.

Inactive ingredients:

Blue pills: carnauba wax, croscarmellose sodium, FD & C Blue No. 2 Aluminum Lake, hypromellose, lactose, magnesium stearate, microcrystalline cellulose, polyethylene glycol, polysorbate 80, purified water, and titanium dioxide.

Dark-green pills: FD & C Blue No. 2 Aluminum Lake, ferric oxide, lactose, magnesium stearate, polyethylene glycol, pregelatinized corn starch, purified water, polyvinyl alcohol, talc, and titanium dioxide.

TriNessa:

Active ingredients: Each white, light-blue, and blue pill contains norgestimate and ethinyl estradiol.

Inactive ingredients:

White pills: carnauba wax, croscarmellose sodium, hypromellose, lactose, magnesium stearate, microcrystalline cellulose, polyethylene glycol, purified water, and titanium dioxide.

Light-blue pills: carnauba wax, croscarmellose sodium, FD & C Blue No. 2 Aluminum Lake, hypromellose, lactose, magnesium stearate, microcrystalline cellulose, polyethylene glycol, purified water, and titanium dioxide.

Blue pills: carnauba wax, croscarmellose sodium, FD & C Blue No. 2 Aluminum Lake, hypromellose, lactose, magnesium stearate, microcrystalline cellulose, polyethylene glycol, polysorbate 80, purified water, and titanium dioxide.

Dark-green pills: FD & C Blue No. 2 Aluminum Lake, ferric oxide, lactose, magnesium stearate, polyethylene glycol, pregelatinized corn starch, purified water, polyvinyl alcohol, talc, and titanium dioxide.

Instructions For Use MonoNessa [mä-nō-nes-a] TriNessa [trī-nes-a] (norgestimate and ethinyl estradiol) Tablets

Important Information about taking MonoNessa or TriNessa

- Take 1 pill every day at the same time. Take the pills in the order directed on your pill dispenser.
- Do not skip your pills, even if you do not have sex often. If you miss pills (including starting the pack late) you could get pregnant. The more pills you miss, the more likely you are to get pregnant.
- If you have trouble remembering to take MonoNessa or TriNessa, talk to your healthcare provider. When you first start taking MonoNessa or TriNessa, spotting or light bleeding in between your periods may occur. Contact your healthcare provider if this does not go away after a few months.
- You may feel sick to your stomach (nauseous), especially during the first few months of taking MonoNessa or TriNessa. If you feel sick to your stomach, do not stop taking the pill. The problem will usually go away. If your nausea does not go away, call your healthcare provider.
- Missing pills can also cause spotting or light bleeding, even when you take the missed pills later. On the days you take 2 pills to make up for missed pills (see What should I do if I miss any MonoNessa or TriNessa pills? below), you could also feel a little sick to your stomach.
- It is not uncommon to miss a period. However, if you miss a period and have not taken MonoNessa or TriNessa according to directions, or miss 2 periods in a row, or feel like you may be pregnant, call your healthcare provider. If you have a positive pregnancy test, you should stop taking MonoNessa or TriNessa.
- If you have vomiting or diarrhea within 3–4 hours of taking your pill, take another pill of the same color from your extra pill dispenser. If you do not have an extra pill dispenser, take the next pill in your pill dispenser. Continue taking all your remaining pills in order. Start the first pill of your next pill dispenser the day after finishing your current pill dispenser. This will be 1 day earlier than originally scheduled. Continue on your new schedule.
- If you have vomiting or diarrhea for more than 1 day, your birth control pills may not work as well. Use an additional birth control method, like condoms and a spermicide, until you check with your healthcare provider.
- Stop taking MonoNessa or TriNessa at least 4 weeks before you have major surgery and do not restart after the surgery without asking your healthcare provider. Be sure to use other forms of contraception (like condoms and spermicide) during this time period.

Before you start taking MonoNessa or TriNessa:

- Decide what time of day you want to take your pill. It is important to take it at the same time every day and in the order as directed on your pill dispenser.
- Have backup contraception (condoms and spermicide) available and if possible, an extra full pack of pills as needed.

When should I start taking MonoNessa or TriNessa?

If you start taking MonoNessa or TriNessa and you have not used a hormonal birth control method before:

- There are 2 ways to start taking your birth control pills. You can either start on a Sunday (Sunday Start) or on the first day (Day 1) of your natural menstrual period (Day 1 Start). Your healthcare provider should tell you when to start taking your birth control pill.
- If you use the Sunday Start, use non-hormonal back-up contraception such as condoms and spermicide for the first 7 days that you take MonoNessa or TriNessa. You do not need back-up contraception if you use the Day 1 Start.

If you start taking MonoNessa or TriNessa and you are switching from another birth control pill:

- Start your new MonoNessa or TriNessa pack on the same day that you would start the next pack of your previous birth control method.
- Do not continue taking the pills from your previous birth control pack.

If you start taking MonoNessa or TriNessa and previously used a vaginal ring or transdermal patch:

- Start using MonoNessa or TriNessa on the day you would have reapplied the next ring or patch.

If you start taking MonoNessa or TriNessa and you are switching from a progestin-only method such as an implant or injection:

- Start taking MonoNessa or TriNessa on the day of removal of your implant or on the day when you would have had your next injection.

If you start taking MonoNessa or TriNessa and you are switching from an intrauterine device or system (IUD or IUS):

- Start taking MonoNessa or TriNessa on the day of removal of your IUD or IUS.
- You do not need back-up contraception if your IUD or IUS is removed on the first day (Day 1) of your period. If your IUD or IUS is removed on any other day, use non-hormonal back-up contraception such as condoms and spermicide for the first 7 days that you take MonoNessa or TriNessa.

Keep a calendar to track your period:

If this is the first time you are taking birth control pills, read, "When should I start taking MonoNessa or TriNessa?" above. Follow these instructions for either a Sunday Start or a Day 1 Start.

Sunday Start:

You will use a Sunday Start if your healthcare provider told you to take your first pill on a Sunday.

- Take pill 1 on the Sunday after your period starts.
- If your period starts on a Sunday, take pill "1" that day and refer to Day 1 Start instructions below.
- Take 1 pill every day in the order on the pill dispenser at the same time each day for 28 days.
- After taking the last pill on Day 28 from the pill dispenser, start taking the first pill from a new pack, on the same day of the week as the first pack (Sunday). Take the first pill in the new pack whether or not you are having your period.
- Use non-hormonal back-up contraception such as condoms and spermicide for the first 7 days of the first cycle that you take MonoNessa or TriNessa.

Day 1 Start:

You will use a Day 1 Start if your doctor told you to take your first pill (Day 1) on the first day of your period.

- Take 1 pill every day in the order of the pill dispenser, at the same time each day, for 28 days.
- After taking the last pill on Day 28 from the pill dispenser, start taking the first pill from a new pack, on the same day of the week as the first pack. Take the first pill in the new pack whether or not you are having your period.

MonoNessa or TriNessa comes in a VERIDATE pill dispenser. Read the instructions below for using your VERIDATE pill dispenser.

Instructions for using your VERIDATE pill dispenser:

- Each VERIDATE pill dispenser has 28 pills. See Figure A.
MonoNessa
  1. 21 blue pills with hormones, for Days 1 to 21
  2. 7 dark green pills (without hormones), for Days 22 to 28
TriNessa
  1. 7 white pills with hormone, for Days 1 to 7
  2. 7 light-blue pills with hormone, for Days 8 to 14
  3. 7 blue pills with hormones, for Days 15 to 21
  4. 7 dark green pills (without hormones), for Days 22 to 28

Figure A

Figure B

Step 1. Place the refill in the VERIDATE Pill Dispenser so that the "V" notch in the refill is at the top of the dispenser. Press the refill down so that it fits firmly under all the nibs. See Figure B.

Figure C

Step 2. Starting your pills.
Sunday Start: Remove the first pill at the top of the dispenser (Sunday) by pressing the pill through the hole in the bottom of the dispenser. See Figure C.

- If your healthcare provider tells you to start taking your pill on Sunday, take your first pill on the first Sunday after your period begins.
- If your period begins on Sunday, take your first pill that day.

Figure D

Day 1 Start:
If you take MonoNessa:

- If your healthcare provider tells you to start taking your pill on "Day 1," choose a blue pill that corresponds with the day of the week on which you are taking the first pill.
- Remove that blue pill by pressing the pill through the hole in the bottom of the dispenser. See Figure D.

Figure E

If you take TriNessa:

- If your healthcare provider tells you to start taking your pill on a day other than Sunday, you will need the calendar label found in your pill package and place it over the calendar in the center of the VERIDATE. See Figure E.

Figure F

- To correctly place the calendar label on the VERIDATE:
  - find your correct starting day
  - find that day printed in blue on the label
  - line your blue starting day up with the first white pill which is directly under the V notch at the top of the dispenser.
- Remove the label from the backing. Press the center of the label down onto the center of the printed calendar.
- Remove that white pill by pressing the pill through the hole in the bottom of the dispenser. See Figure F.

Figure G

Step 3. Continue taking 1 pill every day from the VERIDATE in a clockwise direction until no pills remain in the outer ring. See Figure G.

Figure H

Step 4. The next day take a dark green pill from the inner ring. See Figure H.

- Continue to take a dark green pill each day until all 7 pills are taken.
- During this time your period should begin.

Figure I

Step 5. Insert a new refill:

- After you have taken all the dark green pills, insert a new refill into the VERIDATE and take the first pill on the next day, even if your period is not yet over.
- Lift the empty refill out of the VERIDATE Pill Dispenser. See Figure I.
- Follow the instructions in Step 1 to replace the new refill.

What should I do if I miss any MonoNessa or TriNessa pills?

If you miss 1 pill in Weeks 1, 2, or 3, follow these steps:

- Take it as soon as you remember. Take the next pill at your regular time. This means you may take 2 pills in 1 day.
- Then continue taking 1 pill every day until you finish the pack.
- You do not need to use a back-up birth control method if you have sex.

If you miss 2 pills in Week 1 or Week 2 of your pack, follow these steps:

- Take the 2 missed pills as soon as possible and the next 2 pills the next day.
- Then continue to take 1 pill every day until you finish the pack.
- Use a non-hormonal birth control method (such as a condom and spermicide) as a back-up if you have sex during the first 7 days after missing your pills.

If you miss 2 pills in a row in Week 3, or you miss 3 or more pills in a row during Weeks 1, 2, or 3 of the pack, follow these steps:

- If you are a Day 1 Starter:
  - Throw out the rest of the pill pack and start a new pack that same day.
  - You may not have your period this month but this is expected. However, if you miss your period 2 months in a row, call your healthcare provider because you might be pregnant.
  - You could become pregnant if you have sex during the first 7 days after you restart your pills. You MUST use a non-hormonal birth control method (such as a condom and spermicide) as a back-up if you have sex during the first 7 days after you restart your pills.
- If you are a Sunday Starter:
  - Keep taking 1 pill every day until Sunday. On Sunday, throw out the rest of the pack and start a new pack of pills that same day.
  - Use a non-hormonal birth control method (such as a condom and spermicide) as a back-up if you have sex during the first 7 days after you restart your pills.

If you have any questions or are unsure about the information in this leaflet, call your healthcare provider.

Manufactured by:

JOLLC

Manati, Puerto Rico 00674

Distributed by:

Actavis Pharma, Inc.

Parsippany, NJ 07054 USA

© 2015 Actavis Pharma, Inc.

This Patient Information and Instructions for Use has been approved by the U.S. Food and Drug Administration.

Revised August 2017

Relabeled By: Preferred Pharmaceuticals Inc.

PRINCIPAL DISPLAY PANEL - Kit Carton - TriNessa

Actavis

NDC68788-7239-2

Rx Only

TriNessa®

(norgestimate and ethinyl
estradiol tablets)

28-DAY REGIMEN

Each white tablet contains 0.180 mg norgestimate and 0.035 mg ethinyl
estradiol. Each light blue tablet contains 0.215 mg norgestimate and
0.035 mg ethinyl estradiol. Each blue tablet contains 0.250 mg norgestimate
and 0.035 mg ethinyl estradiol. Each green tablet contains inert ingredients.

Relabeled By: Preferred Pharmaceuticals Inc.